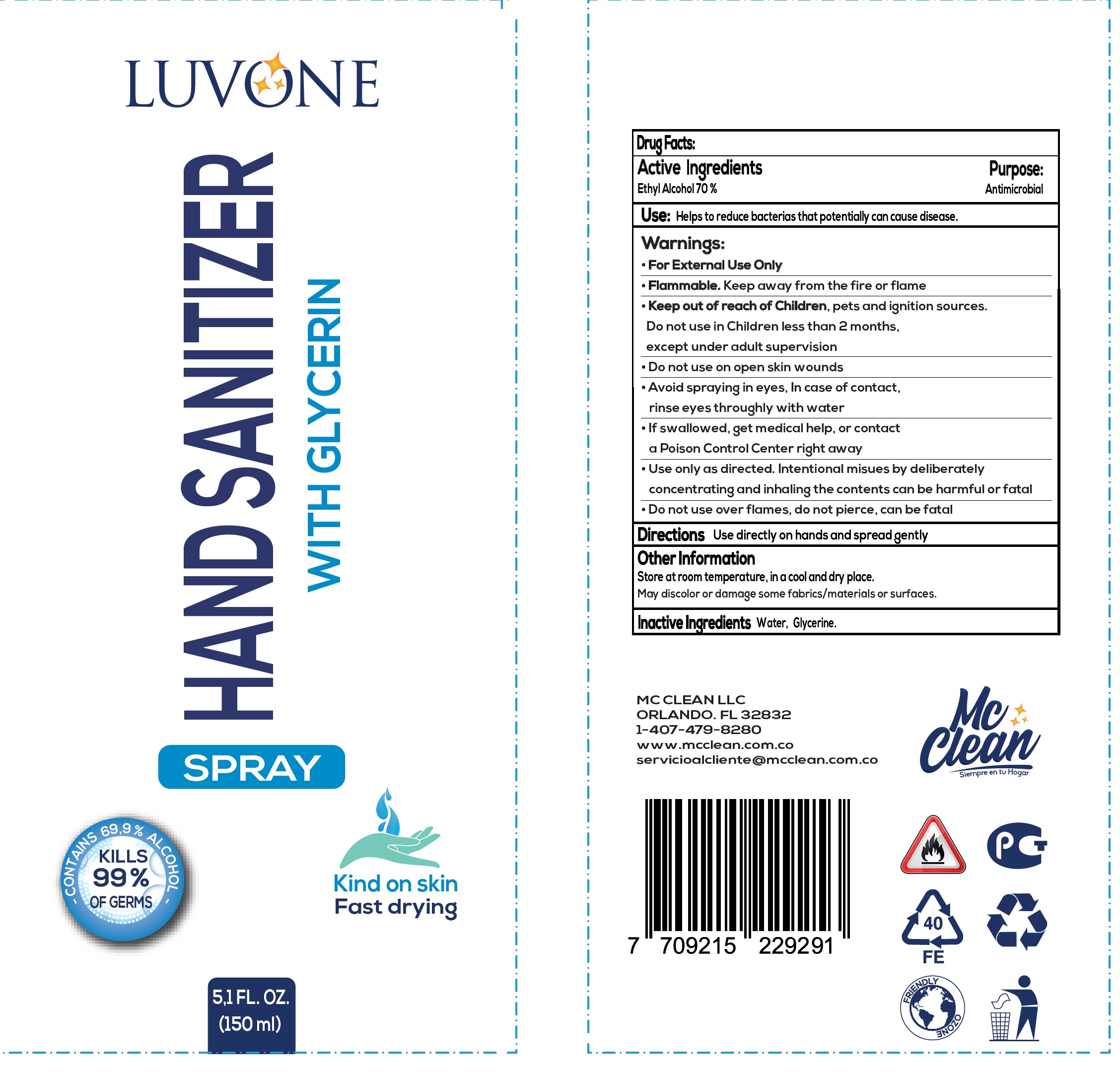 DRUG LABEL: Luvone Hand Sanitizer with glycerin
NDC: 80683-001 | Form: SPRAY
Manufacturer: INDUSTRIAS MC CLEAN S A S
Category: otc | Type: HUMAN OTC DRUG LABEL
Date: 20201222

ACTIVE INGREDIENTS: ALCOHOL 0.7 mL/1 mL
INACTIVE INGREDIENTS: WATER; GLYCERIN

Luvone Hand Sanitizer with glycerin

Active Ingredients

Ethyl Alcohol 70 %

Purpose:

Antimicrobial

Use:

Helps to reduce bacterias that potentially can cause disease.

Warnings:

- For External Use Only
- Flammable. Keep away from the fire or flame

Keep out of reach of Children,

- pets and ignition sources.

Do not use

in Children less than 2 months, except under adult supervision

• Do not use on open skin wounds
• Avoid spraying in eyes, In case of contact, rinse eyes throughly with water
• If swallowed, get medical help, or contact a Poison Control Center right away
• Use only as directed. Intentional misues by deliberately concentrating and inhaling the contents can be harmful or fatal
• Do not use over flames, do not pierce, can be fatal

Directions

Use directly on hands and spread gently

Other Information

Store at room temperature, in a cool and dry place.

May discolor or damage some fabrics/materials or surfaces.

Inactive Ingredients

Water, Glycerine.